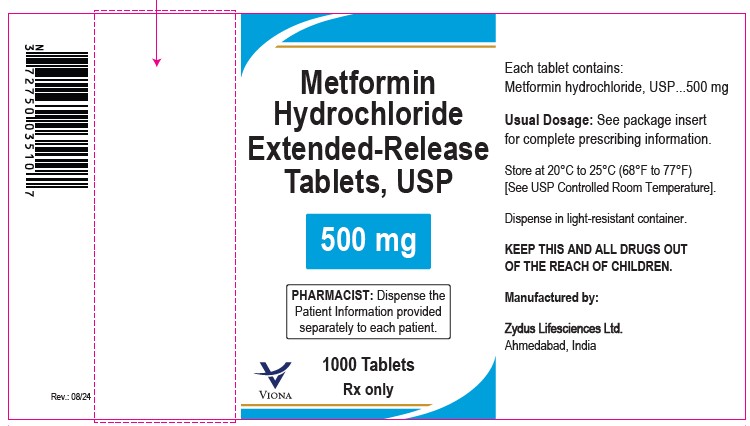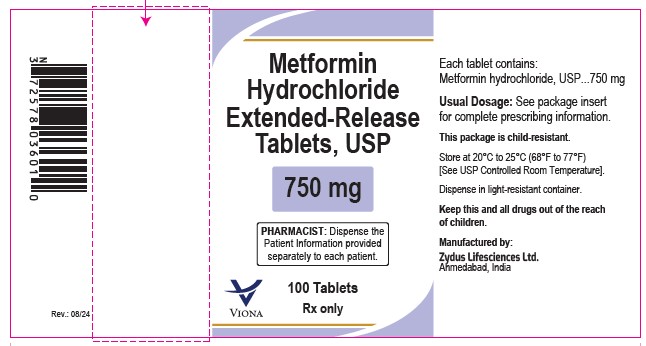 DRUG LABEL: METFORMIN HYDROCHLORIDE
NDC: 65841-027 | Form: TABLET, EXTENDED RELEASE
Manufacturer: Zydus Lifesciences Limited
Category: prescription | Type: HUMAN PRESCRIPTION DRUG LABEL
Date: 20240816

ACTIVE INGREDIENTS: METFORMIN HYDROCHLORIDE 500 mg/1 1
INACTIVE INGREDIENTS: GLYCERYL BEHENATE/EICOSADIOATE; HYPROMELLOSES; POVIDONE; CELLULOSE, MICROCRYSTALLINE

Metformin Hydrochloride Extended-release Tablets, USP

PACKAGE LABEL.PRINCIPAL DISPLAY PANEL

NDC 65841-027-10 in bottle of 1000 tablets

Metformin Hydrochloride Extended-release Tablets USP, 500 mg

Rx only

1000 tablets

NDC 65841-039-01 in bottle of 100 tablets

Metformin Hydrochloride Extended-release Tablets USP, 750 mg

Rx only

100 tablets